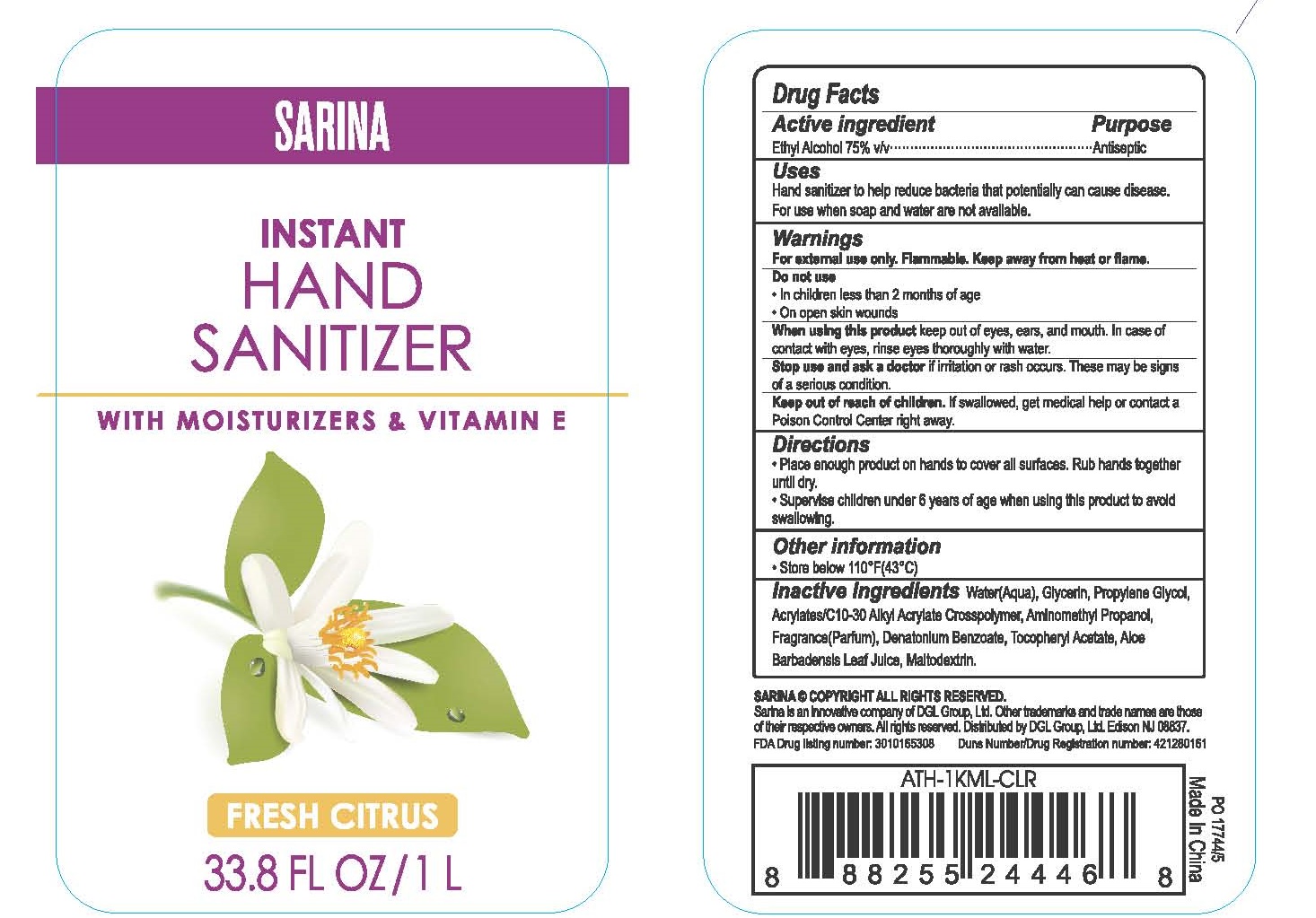 DRUG LABEL: INSTANT HAND SANITIZER
NDC: 76243-338 | Form: GEL
Manufacturer: Dgl Group Ltd.
Category: otc | Type: HUMAN OTC DRUG LABEL
Date: 20201217

ACTIVE INGREDIENTS: ALCOHOL 75 mL/100 mL
INACTIVE INGREDIENTS: MALTODEXTRIN; .ALPHA.-TOCOPHEROL ACETATE; WATER; DENATONIUM BENZOATE; CARBOMER COPOLYMER TYPE A (ALLYL PENTAERYTHRITOL CROSSLINKED); ALOE VERA LEAF; AMINOMETHYLPROPANOL; GLYCERIN; PROPYLENE GLYCOL

SARINA
INSTANT HAND SANITIZER

Active ingredient

Ethyl Alcohol 75% v/v

Purpose

Antiseptic

Uses

- Hand sanitizer to help reduce bacteria that potentially can cause disease.
- For use when soap and water are not available.

Warnings

For external use only. Flammable. Keep away from heat or flame.

Do not use

- In children less than 2 months of age
- On open skin wounds

When using this product

- keep out of eyes, ears, and mouth.
- In case of contact with eyes, rinse eyes thoroughly with water.

Stop use and ask a doctor

if irritation or rash occurs. These may be signs of a serious condition.

Keep out of reach of children

If swallowed, get medical help or contact a Poison Control Center right away.

Directions

- Place enough product on hands to cover all surfaces. Rub hands together until dry.
- Supervise children under 6 years of age when using this product to avoid swallowing.

Other information

- Store below 110 °F(43℃)

Inactive ingredients

Water(Aqua), Glycerin, Propylene Glycol, Acrylates/C 10-30 Alkyl Acrylate Crosspolymer, Aminomethyl Propanol, Fragrance(Parfum), Denatonium Benzoate, Tocopheryl Acetate, Aloe Barbadensis Leaf Juice, Maltodextrin.